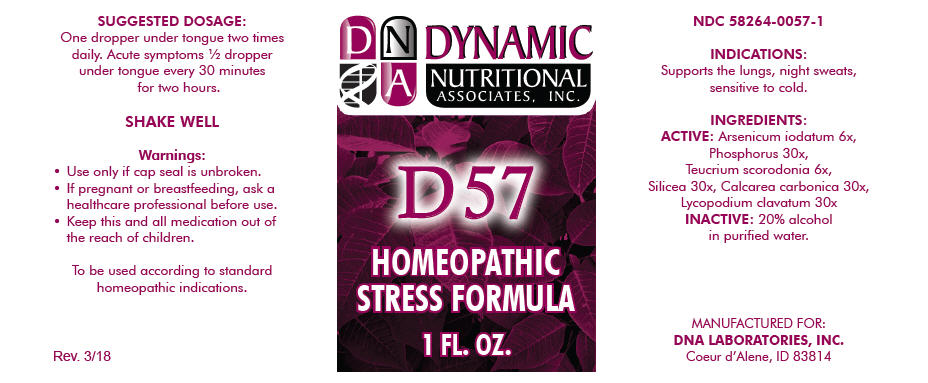 DRUG LABEL: D-57
NDC: 58264-0057 | Form: SOLUTION
Manufacturer: DNA Labs, Inc.
Category: homeopathic | Type: HUMAN OTC DRUG LABEL
Date: 20250113

ACTIVE INGREDIENTS: ARSENIC TRIIODIDE 6 [hp_X]/1 mL; PHOSPHORUS 30 [hp_X]/1 mL; TEUCRIUM SCORODONIA FLOWERING TOP 6 [hp_X]/1 mL; SILICON DIOXIDE 30 [hp_X]/1 mL; OYSTER SHELL CALCIUM CARBONATE, CRUDE 30 [hp_X]/1 mL; LYCOPODIUM CLAVATUM SPORE 30 [hp_X]/1 mL
INACTIVE INGREDIENTS: ALCOHOL; WATER

D-57

NDC 58264-0057-1

INDICATIONS

PURPOSE

Supports the lungs, night sweats, sensitive to cold.

INGREDIENTS

ACTIVE

Arsenicum iodatum 6x, Phosphorus 30x, Teucrium scorodonia 6x, Silicea 30x, Calcarea carbonica 30x, Lycopodium clavatum 30x

INACTIVE

20% alcohol in purified water.

SUGGESTED DOSAGE

One dropper under tongue two times daily. Acute symptoms ½ dropper under tongue every 30 minutes for two hours.

STORAGE AND HANDLING

SHAKE WELL

Warnings

- Use only if cap seal is unbroken.

PREGNANCY OR BREAST FEEDING

- If pregnant or breastfeeding, ask a healthcare professional before use.

KEEP OUT OF REACH OF CHILDREN

- Keep this and all medication out of the reach of children.

To be used according to standard homeopathic indications.

PRINCIPAL DISPLAY PANEL - 1 FL. OZ. Bottle Label

DYNAMIC
NUTRITIONAL
ASSOCIATES, INC.

D 57

HOMEOPATHIC
STRESS FORMULA

1 FL. OZ.